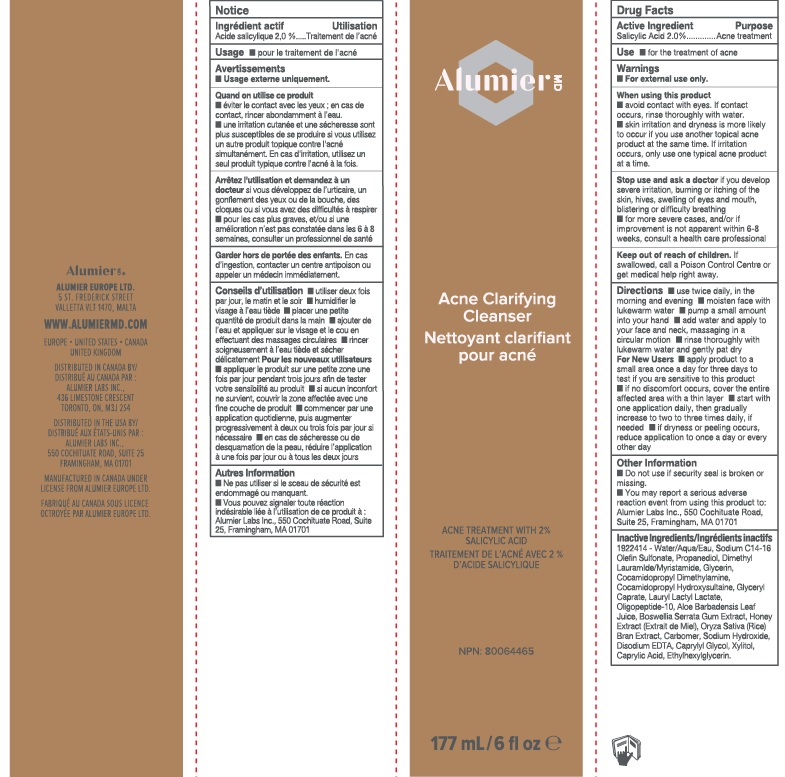 DRUG LABEL: Alumier MD Acne Clarifying Cleanser
NDC: 69473-001 | Form: GEL
Manufacturer: Alumier Labs
Category: otc | Type: HUMAN OTC DRUG LABEL
Date: 20241201

ACTIVE INGREDIENTS: SALICYLIC ACID 20 mg/1 mL
INACTIVE INGREDIENTS: CAPRYLIC ACID; PROPANEDIOL; COCAMIDOPROPYL HYDROXYSULTAINE; GLYCERYL CAPRATE; OLIGOPEPTIDE-10; HONEY; EDETATE DISODIUM; COCAMIDOPROPYL DIMETHYLAMINE; ALOE VERA LEAF; CAPRYLYL GLYCOL; GLYCERIN; RICE BRAN; CARBOXYPOLYMETHYLENE; SODIUM HYDROXIDE; XYLITOL; ETHYLHEXYLGLYCERIN; INDIAN FRANKINCENSE; WATER; SODIUM C14-16 OLEFIN SULFONATE

Alumier MD Acne Clarifying Cleanser

Active Ingredient

Salicylic Acid 2.0%

Purpose

Acne Treatment

Use

- for the treatment of acne

Warnings

- For external use only.

When using this product

- avoid contact with eyes. If contact occurs, rinse thoroughly with water.
- skin irritation and dryness is more likely to occur if you use another topical acne product at the same time. If irritation occurs, only use one topical acne product at a time.

Stop use and ask a doctor if you develop severe irritation, burning or itching of the skin, hives, swelling of eyes and mouth, blistering or difficulty breathing

- for more severe cases, and/or if improvement is not apparent within 6-8 weeks, consult a health care professional

Keep out of reach of children. If swallowed, call a Poison Control Centre or get medical help right away.

Directions

- use twice daily, in the morning and evening
- moisten face with lukewarm water
- pump a small amount into your hand
- add water and apply to your face and neck, massaging in a circular motion
- rinse thoroughly with lukewarm water and gently pat dry

For New Users

- apply product to a small area once a day for three days to test if you are sensitive to this product
- if no discomfort occurs, cover the entire affected area with a thin layer
- start with one application daily, then gradually increase to two to three times daily, if needed
- if dryness or peeling occurs, reduce application to once a day or every other day

Other Information

- Do not use if security seal is broken or missing
- You may report a serious adverse reaction event from using this product to: Alumier Labs Inc., 550 Cochituate Road, Suite 25, Framingham, MA 01701

Inactive Ingredients

Water/Aqua/Eau, Sodium C14-16 Olefin Sulfonate, Propanediol, Dimethyl Lauramide/Myristamide, Glycerin, Cocamidopropyl Dimethylamine, Cocamidopropyl Hydroxysultaine, Glyceryl Caprate, Lauryl Lactyl Lactate, Oligopeptide-10, Aloe Barbadensis Leaf Juice, Boswellia Serrata Gum Extract, Honey Extract (Extrait de Miel), Oryza Sativa (Rice) Bran Extract, Carbomer, Sodium Hydroxide, Disodium EDTA, Caprylyl Glycol, Xylitol, Caprylic Acid, Ethylhexylglycerin.

Company Information

ALUMIER EUROPE LTD.

5 ST. FREDERICK STREET

VALLETTA VLT 1470, MALTA

WWW.ALUMIERMD.COM

EUROPE • UNITED STATES • CANADA

UNITED KINGDOM

DISTRIBUTED IN CANADA BY

ALUMIER LABS INC.,

436 LIMESTONE CRESCENT

TORONTO, ON, M3J 2S4

DISTRIBUTED IN THE USA BY

ALUMIER LABS INC.,

550 COCHITUATE ROAD, SUITE 25

FRAMINGHAM, MA 01701

MANUFACTURED IN CANADA UNDER

LICENSE FROM ALUMIER EUROPE LTD.

Product Packaging

Alumier MD

Acne Clarifying Cleanser

ACNE TREATMENT WITH 2%

SALICYLIC ACID

NPN: 80064465

177 mL/6 fl oz